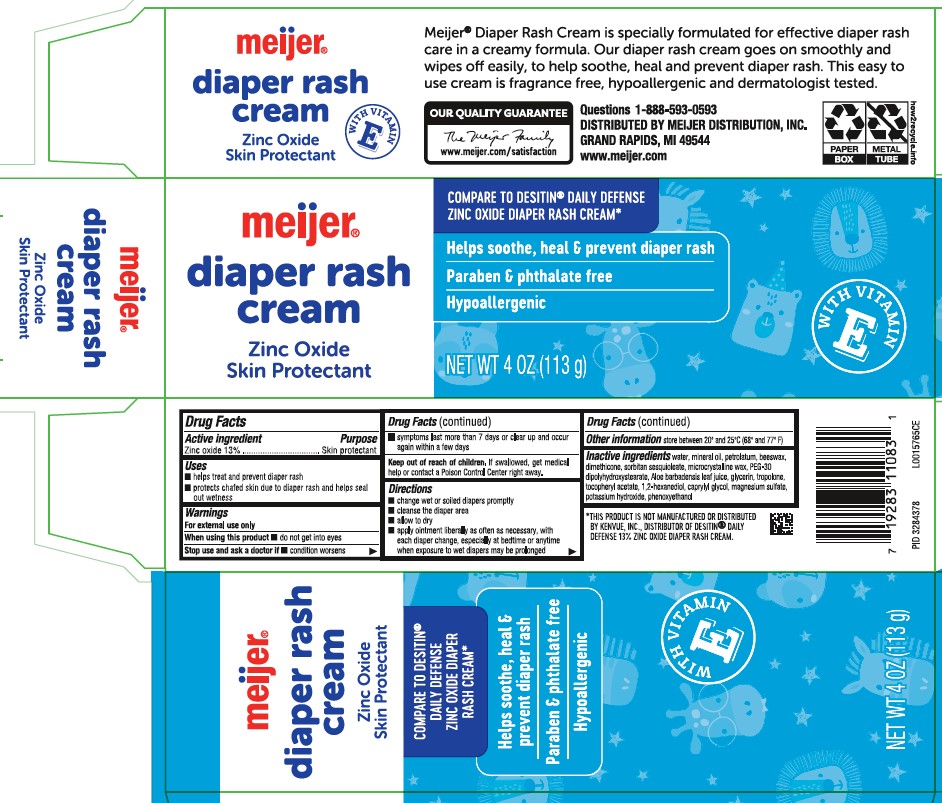 DRUG LABEL: Baby Diaper Rash
NDC: 41250-226 | Form: OINTMENT
Manufacturer: Meijer, Inc.
Category: otc | Type: HUMAN OTC DRUG LABEL
Date: 20260219

ACTIVE INGREDIENTS: ZINC OXIDE 130 mg/1 g
INACTIVE INGREDIENTS: WATER; MINERAL OIL; PETROLATUM; YELLOW WAX; DIMETHICONE; SORBITAN SESQUIOLEATE; MICROCRYSTALLINE WAX; PEG-30 DIPOLYHYDROXYSTEARATE; ALOE VERA LEAF; GLYCERIN; TROPOLONE; .ALPHA.-TOCOPHEROL ACETATE; 1,2-HEXANEDIOL; CAPRYLYL GLYCOL; MAGNESIUM SULFATE MONOHYDRATE; POTASSIUM HYDROXIDE; PHENOXYETHANOL

Meijer 226.002/226AD
Creamy Diaper Rash Ointment

Active ingredient

Zinc oxide 13%

Purpose

Skin protectant

Uses

- helps treat and prevent diaper rash
- protects chafed skin due to diaper rash and helps seal out wetness

Warnings

For extenal use only

When using this product

- do not get into eyes

Stop use and ask a doctor if

- condition worsens
- symptoms last more than 7 days or clear up and occur again within a few days

Keep out of reach of children.

If swallowed, get medical help or contact a Poison Control Center right away.

Directions

- change wet or soiled diapers promptly
- cleanse the diaper area
- allow to dry
- apply ointment liberally as often as necessary, with each diaper change, especially at bedtime or anytime when exposure to wet diapers may be prolonged

Other information

store between 20° and 25°C (68° and 77°F)

Inactive ingredients

water, mineral oil, petrolatum, beeswax, dimethicone, sorbitan sesquioleate, microcrystalline wax, PEG-30 dipolyhydroxystearate, Aloe barbadensis leaf juice, glycerin, tropolone, tocopheryl acetate, 1,2-hexanediol, caprylyl glycol, magnesium sulfate, potassium hydroxide, phenoxyethanol

Disclaimer

*THIS PRODUCT IS NOT MANUFACTURED OR DISTRIBUTED BY KENVUE, INC., DISTRIBUTOR OF DESITIN® DAILY DEFENSE 13% ZINC OXIDE DIAPER RASH CREAM.

Claims

meijer®

diaper rash cream

Zinc Oxide

Skin Protectant

WITH VITAMIN E

Meijer® Diaper Rash Cream is specially formulated for effective diaper rash care in a creamy formula. Our diaper rash cream goes on smoothly and wipes off easily, to help soothe, heal and prevent diaper rash. This easy to use cream is fragrancec free, hypoallergenic and dermatologist tested.

Adverse reactions

OUR QUALITY GUARANTEE

The Meijer Family

www.meijer.com/satisfaction

Questions 1-888-593-0593

DISTRIBUTED BY MEIJER DISTRIBUTION, INC.

GRAND RAPIDS, MI 49544

www.meijer.com

Principal display panel

meijer®

diaper rash cream

Zinc Oxide

Skin Protectant

COMPARE TO DESITIN® DAILY DEFENSE ZINC OXIDE DIAPER RASH CREAM*

Helps soothe, heal & prevent diaper rash

Paraben & phthalate free

Hypoallergenic

WITH VITAMIN E

NET WT 4 OZ (113 g)